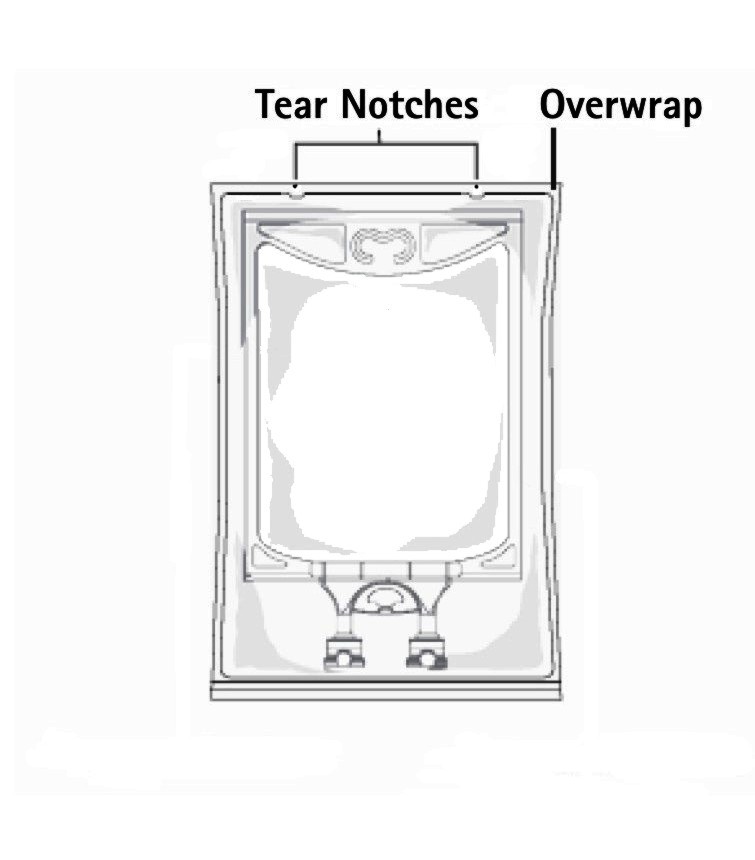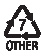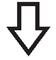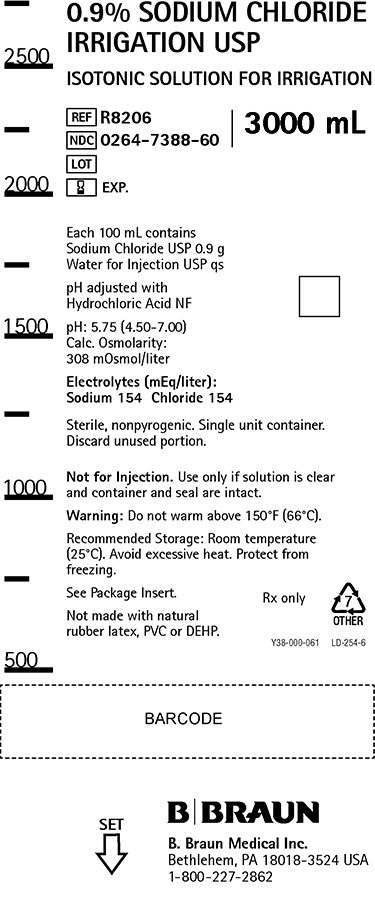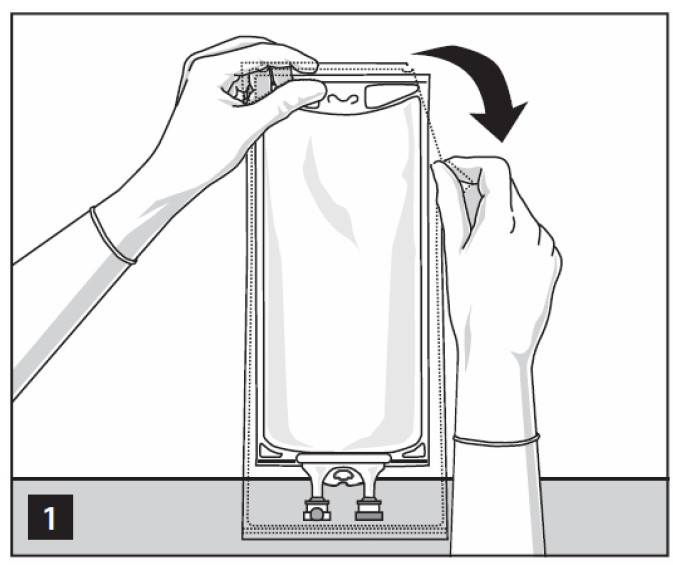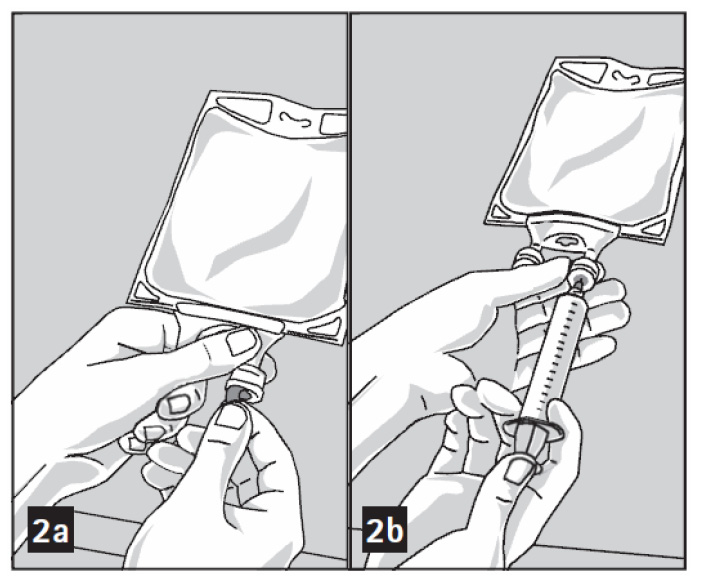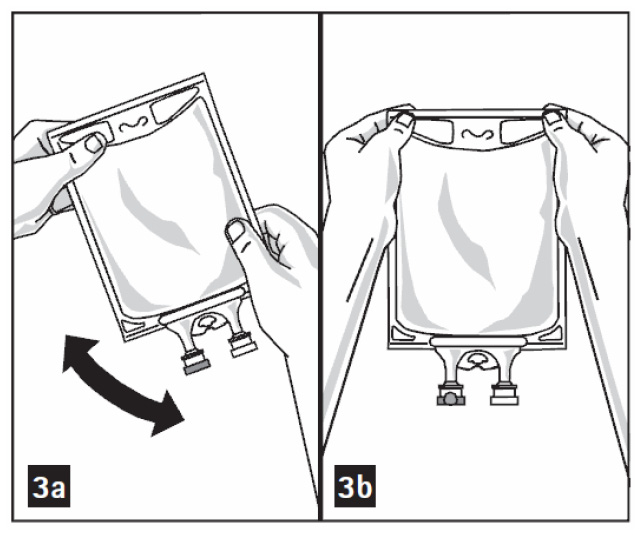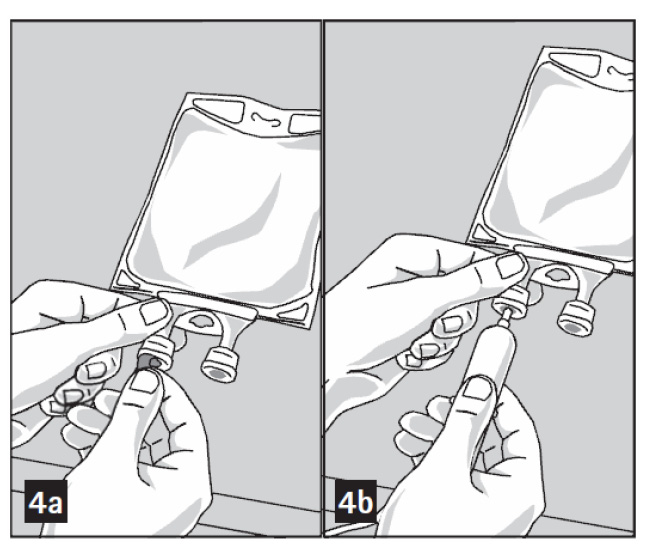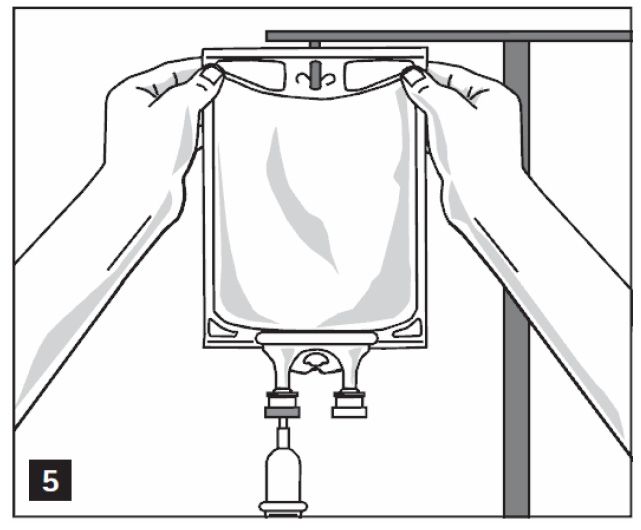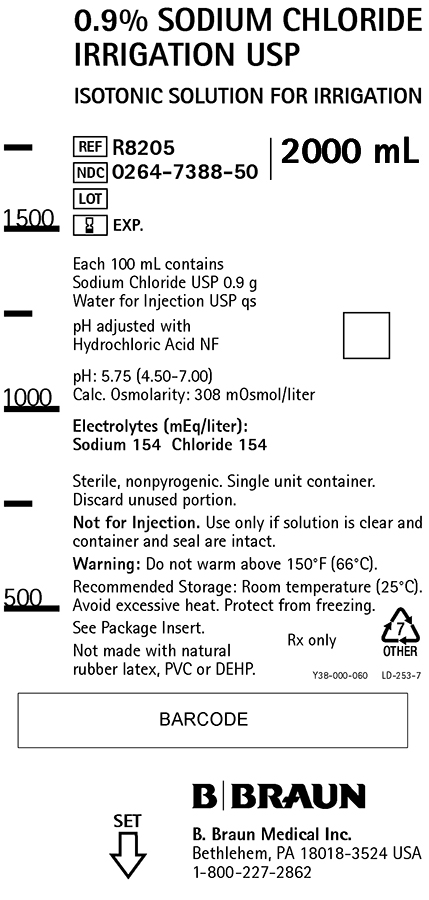 DRUG LABEL: Sodium Chloride for Irrigation
NDC: 0264-7388 | Form: SOLUTION
Manufacturer: B. Braun Medical Inc.
Category: prescription | Type: HUMAN PRESCRIPTION DRUG LABEL
Date: 20210806

ACTIVE INGREDIENTS: SODIUM CHLORIDE 0.9 g/100 mL
INACTIVE INGREDIENTS: WATER

0.9% Sodium Chloride Irrigation USP

Isotonic Solution for Irrigation.

For Irrigation Only.

Not for Injection.

DESCRIPTION

Each 100 mL contains:

Sodium Chloride USP 0.9 g; Water for Injection USP qs

pH adjusted with Hydrochloric Acid NF

pH: 5.75 (4.50-7.00)

Calculated Osmolarity: 308 mOsmol/liter

Concentration of Electrolytes (mEq/liter): Sodium 154; Chloride 154

0.9% Sodium Chloride Irrigation USP is sterile, nonpyrogenic, isotonic and contains no bacteriostatic or antimicrobial agents.

The formula of the active ingredient is:

Ingredient | Molecular Formula | Molecular Weight
Sodium Chloride USP | NaCl | 58.44

The plastic container is made from a multilayered film specifically developed for parenteral drugs. It contains no plasticizers and exhibits virtually no leachables. The solution contact layer is a rubberized copolymer of ethylene and propylene. The container is nontoxic and biologically inert. The container-solution unit is a closed system and is not dependent upon entry of external air during administration. The container is overwrapped to provide protection from the physical environment and to provide an additional moisture barrier when necessary.

Not made with natural rubber latex, PVC or DEHP.

CLINICAL PHARMACOLOGY

0.9% Sodium Chloride Irrigation USP is utilized for a variety of clinical indications such as sterile irrigation of body cavities, tissues or wounds, indwelling urethral catheters, surgical drainage tubes, and for washing, rinsing or soaking surgical dressings, instruments and laboratory specimens. It also serves as a diluent or vehicle for drugs used for irrigation or other pharmaceutical preparations.

0.9% Sodium Chloride Irrigation USP provides an isotonic saline irrigation identical in composition with 0.9% Sodium Chloride Injection USP (normal saline).

Physiological irrigation solutions are considered generally compatible with living tissues and organs.

Sodium, the major cation of the extracellular fluid, functions primarily in the control of water distribution, fluid balance, and osmotic pressure of body fluids. Sodium is also associated with chloride and bicarbonate in the regulation of the acid-base equilibrium of body fluid.

Chloride, the major extracellular anion, closely follows the metabolism of sodium, and changes in the acid-base balance of the body are reflected by changes in the chloride concentration.

INDICATIONS AND USAGE

0.9% Sodium Chloride Irrigation USP is indicated for all general irrigation, washing, rinsing and dilution purposes which permit use of a sterile, nonpyrogenic electrolyte solution.

CONTRAINDICATIONS

0.9% Sodium Chloride Irrigation USP is not for injection by usual parenteral routes.

An electrolyte solution should not be used for irrigation during electrosurgical procedures.

WARNINGS

FOR IRRIGATION ONLY. NOT FOR INJECTION.

Irrigating fluids have been demonstrated to enter the systemic circulation in relatively large volumes; thus, irrigation solutions must be regarded as systemic drugs. Absorption of large amounts can cause fluid and/or solute overload resulting in dilution of serum electrolyte concentrations, overhydration, congested states or pulmonary edema.

The risk of dilutional states is inversely proportional to the electrolyte concentrations of the administered parenteral solutions. The risk of solute overload causing congested states with peripheral and pulmonary edema is directly proportional to the electrolyte concentration.

Do not warm above 150°F (66°C).

After opening container, its contents should be used promptly to minimize the possibility of bacterial growth or pyrogen formation.

Discard unused portion of irrigating solution since it contains no preservatives.

PRECAUTIONS

General

Use aseptic technique when preparing and administering sterile irrigation solutions.

Use only if solution is clear and container and seal are intact.

Do not use for irrigation that may result in absorption of large amounts of fluid into the blood.

Caution should be observed when the solution is used for continuous irrigation or allowed to ‘‘dwell” inside body cavities because of possible absorption into the blood stream and the production of circulatory overload.

When used for irrigation via appropriate irrigation equipment, the administration set should be attached promptly. Unused portions should be discarded and a fresh container of appropriate size used for the start up of each cycle or repeat procedure. For repeated irrigations of urethral catheters, a separate container should be used for each patient.

Laboratory Tests

Clinical evaluation and periodic laboratory determinations are necessary to monitor changes in fluid balance, electrolyte concentrations, and acid-base balance after prolonged irrigation, when fluid absorption is suspected, or whenever the condition of the patient warrants such evaluation.

Drug Interactions

Some additives may be incompatible. Consult with pharmacist. When introducing additives, use aseptic technique. Mix thoroughly. Do not store.

Carcinogenesis, Mutagenesis, Impairment of Fertility

Studies with 0.9% Sodium Chloride Irrigation USP have not been performed to evaluate carcinogenic potential, mutagenic potential, or effects on fertility.

Pregnancy

Teratogenic Effects

Animal reproduction studies have not been conducted with 0.9% Sodium Chloride Irrigation USP. It is also not known whether 0.9% Sodium Chloride Irrigation USP can cause fetal harm when administered to a pregnant woman or can affect reproduction capacity. 0.9% Sodium Chloride Irrigation USP should be given to a pregnant woman only if clearly needed.

Labor and Delivery

Safety and effectiveness of 0.9% Sodium Chloride Irrigation USP during labor and delivery have not been established. Caution should be exercised, and the fluid balance, glucose and electrolyte concentrations, and acid-base balance, of both mother and fetus should be evaluated periodically or whenever warranted by the condition of the patient or fetus.

Nursing Mothers

It is not known whether this drug is excreted in human milk. Because many drugs are excreted in human milk, caution should be exercised when 0.9% Sodium Chloride Irrigation USP is administered to a nursing woman.

Pediatric Use

The safety and effectiveness of 0.9% Sodium Chloride Irrigation USP in pediatric patients have not been established. Its limited use in pediatric patients has been inadequate to fully define proper dosage and limitations for use.

Geriatric Use

Clinical studies of 0.9% Sodium Chloride Irrigation USP did not include a sufficient number of patients age 65 years and over to determine whether they respond differently from younger subjects. In general, dose selection for an elderly patient should be cautious, usually starting at the low end of the dosing range, reflecting the greater frequency of decreased hepatic, renal, or cardiac function, and of concomitant disease or other drug therapy.

This drug is known to be substantially excreted by the kidney, and the risk of toxic reactions to this drug may be greater in patients with impaired renal function. Because elderly patients are more likely to have decreased renal function, care should be taken in dose selection, and it may be useful to monitor renal function. Frequent laboratory determinations and clinical evaluations are recommended to monitor changes in blood glucose, electrolyte concentrations, and renal function.

ADVERSE REACTIONS

Possible adverse effects arising from the irrigation of body cavities, tissues, or indwelling catheters and tubes can be minimized when proper procedures are followed. Displaced catheters or drainage tubes can lead to irrigation or infiltration of unintended structures or cavities. Excessive volume or pressure during irrigation of closed cavities may cause undue distension or disruption of tissues. Accidental contamination from careless technique may transmit infection.

If an adverse reaction does occur, discontinue administration of the irrigant, evaluate the patient, institute appropriate therapeutic countermeasures, and save the remainder of the fluid for examination if deemed necessary.

OVERDOSAGE

In the event of overhydration or solute overload, reevaluate the patient’s condition, and institute appropriate corrective treatment. Intravascular volume overload may respond to hemodialysis. See WARNINGS, PRECAUTIONS, and ADVERSE REACTIONS.

DOSAGE AND ADMINISTRATION

As required for irrigation.

When used as a diluent, or vehicle for other drugs, the drug manufacturer's recommendations should be followed.

Some additives may be incompatible. Consult with pharmacist. When introducing additives, use aseptic techniques. Mix thoroughly. Do not store.

Solutions should be inspected visually for particulate matter and discoloration prior to administration, whenever solution and container permits.

HOW SUPPLIED

0.9% Sodium Chloride Irrigation USP is supplied sterile and nonpyrogenic in single-dose 2000 mL and 3000 mL plastic containers packaged 4 per case.

NDC | REF | SIZE
0264-7388-50 | R8205 | 2000 mL
0264-7388-60 | R8206 | 3000 mL

Exposure of pharmaceutical products to heat should be minimized. Avoid excessive heat. Protect from freezing. It is recommended that the product be stored at room temperature (25°C); however, brief exposure up to 40°C does not adversely affect the product.

Do not warm above 150°F (66°C).

Directions for Use of Plastic Container

Not for injection.

Not for use with pressurized irrigation systems.

Aseptic technique is required.

- Inspect irrigation bag: overwrap and primary bag.
- Do not use if overwrap has been damaged.
- Do not use unless solution is clear and closure is intact.

1. To open: Tear overwrap starting from the tear notches. (Figure 1)
2. Prepare medication port by removal of aluminum foil. (Figure 2a)
  - Puncture resealable medication port by using 19 – 22 gauge needle and inject additive(s). (Figure 2b)
  - Mix solution and medication thoroughly. (Figure 3a)
  - Medication port must be swabbed with disinfection agent (e.g. iso-propanol or chlorhexidine) before re-puncturing.
  - Check admixture visually for particulate matter. (Figure 3b)
3. Remove aluminum foil from outlet/set port at the bottom of container (Figure 4a) and attach administration set (Figure 4b): use non-vented infusion set or close air vent on a vented set. Refer to directions for use accompanying the administration set.
4. Hang bag on IV Pole. (Figure 5)

Y36-002-963 LD-398-4

Package Insert

Rx only

Revised: June 2018

B. Braun Medical Inc.
Bethlehem, PA 18018-3524 USA
1-800-227-2862

PRINCIPAL DISPLAY PANEL - 2000 mL Container Label

0.9% SODIUM CHLORIDE IRRIGATION USP

ISOTONIC SOLUTION FOR IRRIGATION

REF R8205
NDC 0264-7388-50
LOT
EXP.

2000 mL

Each 100 mL contains
Sodium Chloride USP 0.9 g
Water for Injection USP qs

pH adjusted with
Hydrochloric Acid NF

pH: 5.75 (4.50-7.00)
Calc. Osmolarity: 308 mOsmol/liter

Electrolytes (mEq/liter):
Sodium 154 Chloride 154

Sterile, nonpyrogenic. Single unit container.
Discard unused portion.

Not for Injection. Use only if solution is clear and
container and seal are intact.

Warning: Do not warm above 150°F (66°C).

Recommended Storage: Room temperature (25°C).
Avoid excessive heat. Protect from freezing.

See Package Insert.

Not made with natural
rubber latex, PVC or DEHP.

Rx only

Y38-000-060 LD-253-7

B. Braun Medical Inc.
Bethlehem, PA 18018-3524 USA
1-800-227-2862

SET

0.9% Sodium Chloride Irrigation 2L Container Label

PRINCIPAL DISPLAY PANEL - 3000 mL Container Label

0.9% SODIUM CHLORIDE IRRIGATION USP

ISOTONIC SOLUTION FOR IRRIGATION

REF R8206
NDC 0264-7388-60
LOT
EXP.

3000 mL

Each 100 mL contains
Sodium Chloride USP 0.9 g
Water for Injection USP qs

pH adjusted with
Hydrochloric Acid NF

pH: 5.75 (4.50-7.00)
Calc. Osmolarity:
308 mOsmol/liter

Electrolytes (mEq/liter):
Sodium 154 Chloride 154

Sterile, nonpyrogenic. Single unit container. Discard
unused portion.

Not for Injection. Use only if solution is clear
and container and seal are intact.

Warning: Do not warm above 150°F (66°C).

Recommended Storage: Room temperature
(25°C). Avoid excessive heat. Protect from
freezing.

See Package Insert.

Not made with natural
rubber latex, PVC or DEHP.

Rx only

Y38-000-061 LD-254-6

B. Braun Medical Inc.
Bethlehem, PA 18018-3524 USA
1-800-227-2862

SET

0.9% Sodium Chloride Irrigation 3L Container Label